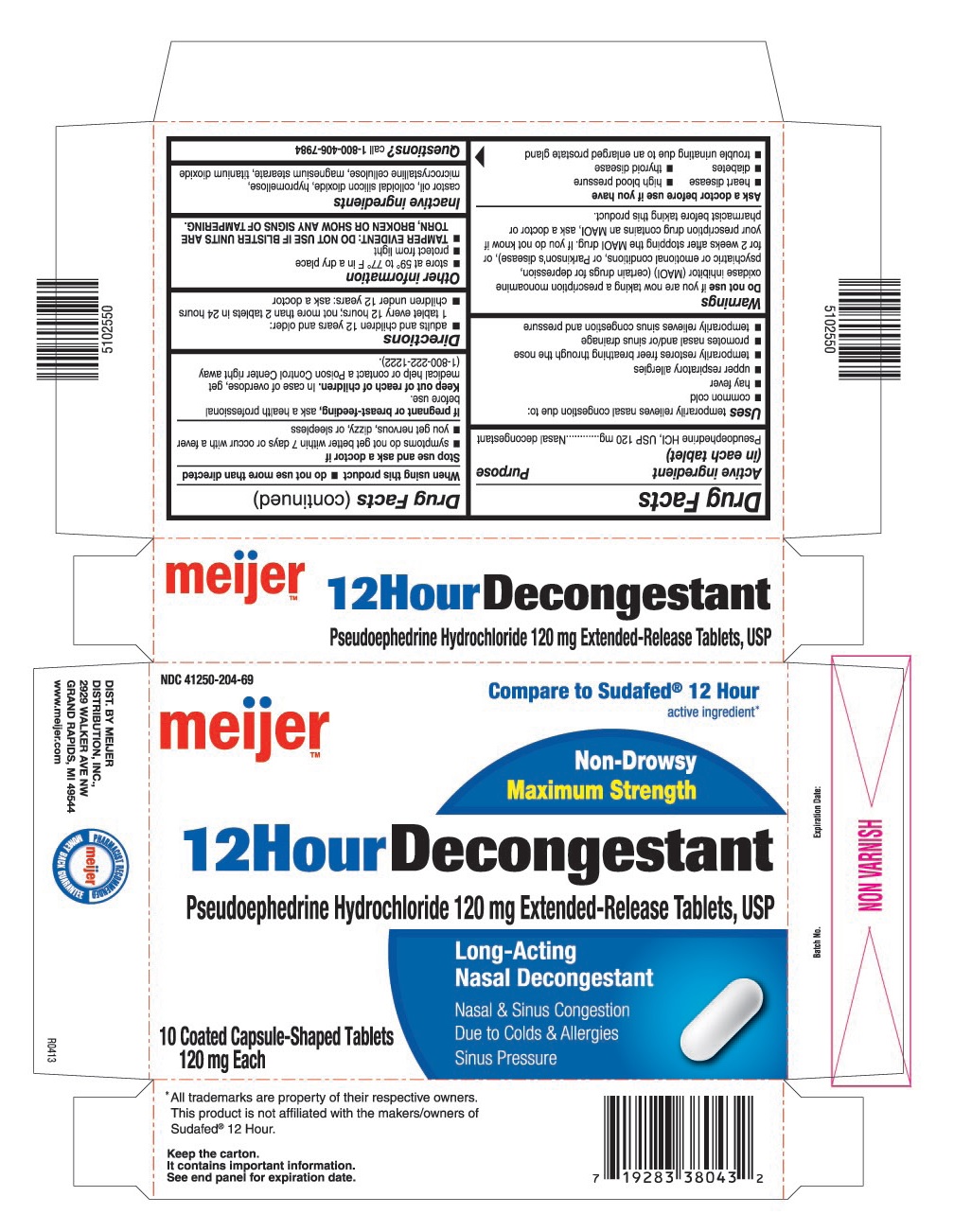 DRUG LABEL: Pseudoephedrine Hydrochloride
NDC: 41250-204 | Form: TABLET, FILM COATED, EXTENDED RELEASE
Manufacturer: Meijer Distribution, Inc.
Category: otc | Type: HUMAN OTC DRUG LABEL
Date: 20130507

ACTIVE INGREDIENTS: PSEUDOEPHEDRINE HYDROCHLORIDE 120 mg/1 1
INACTIVE INGREDIENTS: CASTOR OIL; COLLOIDAL SILICON DIOXIDE; HYPROMELLOSES; CELLULOSE, MICROCRYSTALLINE; MAGNESIUM STEARATE; TITANIUM DIOXIDE

Drug Facts

ACTIVE INGREDIENT (IN EACH TABLET)

Pseudoephedrine HCl USP, 120 mg

PURPOSE

Nasal decongestant

USES

Temporarily relieves nasal congestion due to:

- common cold
- hay fever
- upper respiratory allergies
- temporarily restores freer breathing through the nose
- promotes nasal and/or sinus drainage
- temporarily relieves sinus congestion and pressure

WARNINGS

Do not use

If you are now taking a prescription monoamine oxidase inhibitor (MAOI) (certain drugs for depression, psychiatric or emotional conditions, or Parkinson's disease), or for 2 weeks after stopping the MAOI drug. If you do not know if your prescription drug contains an MAOI, ask a doctor or pharmacist before taking this product.

Ask a doctor before use if you have

- heart disease
- high blood pressure
- diabetes
- thyroid disease
- trouble urinating due to an enlarged prostate gland

When using this product

- do not use more than directed

Stop use and ask a doctor if

- symptoms do not get better within 7 days or occur with a fever
- you get nervous, dizzy, or sleepless

If pregnant or breast-feeding

Ask a health professional before use.

Keep out of reach of children.

In case of overdose, get medical help or contact a Poison Control Center right away.

DIRECTIONS

- adults and children 12 years and older: 1 tablet every 12 hours; not more than 2 tablets in 24 hours
- children under 12 years: ask a doctor

OTHER INFORMATION

- store at 59° to 77° F in a dry place
- protect from light
- TAMPER EVIDENT: DO NOT USE IF BLISTER UNITS ARE TORN, BROKEN OR SHOW ANY SIGNS OF TAMPERING.

INACTIVE INGREDIENTS

Castor oil, colloidal silicon dioxide, hypromellose, microcrystalline cellulose, magnesium stearate, titanium dioxide

QUESTIONS?

Call 1-800-406-7984

PRINCIPAL DISPLAY PANEL

NDC 41250-204-69

Compare to Sudafed® 12 Hour active ingredient*

meijer™

Non-Drowsy

Maximum Strength

12 Hour Decongestant

Pseudoephedrine Hydrochloride 120 mg Extended-Release Tablets, USP

Long-Acting

Nasal Decongestant

Nasal & Sinus Congestion

Due to Colds & Allergies

Sinus Pressure

10 Coated Capsule-Shaped Tablets

120 mg Each

DIST. BY MEIJER

5102550/R0413